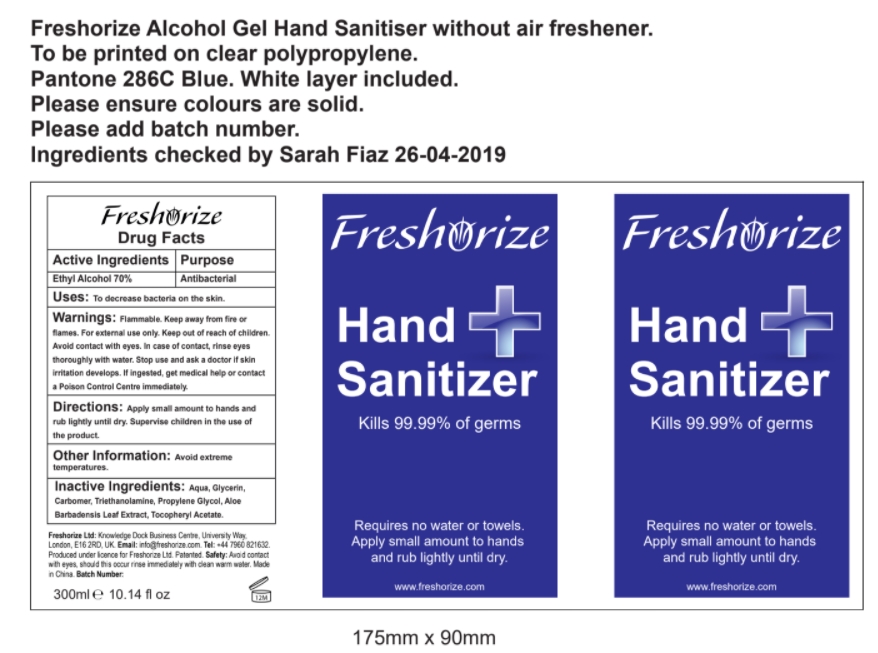 DRUG LABEL: Ethyl Alcohol
NDC: 52305-001 | Form: GEL
Manufacturer: Freshorize LTD
Category: otc | Type: HUMAN OTC DRUG LABEL
Date: 20210317

ACTIVE INGREDIENTS: ALCOHOL 70 mL/100 mL
INACTIVE INGREDIENTS: PROPYLENE GLYCOL 0.001 mL/100 mL; CARBOMER 934 0.28 mL/100 mL; .ALPHA.-TOCOPHEROL ACETATE 0.001 mL/100 mL; WATER 37.307 mL/100 mL; GLYCERIN 0.3 mL/100 mL; ALOE VERA LEAF 0.001 mL/100 mL

Freshorize Gel Hand Sanitizer

Inactive Ingredients

Water (Aqua), Glycertin, Carbomer, Propylene Glycol, Aloe Barbadensis Leaf Extract, Tocopheryl Acetate

Directions

Apply small amount ot hands and rub lightly until dry.

Supervise children in the use of the product.

Warnings:

Flammable. Keep away from fire or flames. For external use only.
Keep out of reach of children.
Avoid contact with eyes.
In case of contact, rinse eyes throroughly with water.
Stop use and ask a doctor if skin irritation develops.
If ingested, get medical help or contact a
Poison Control Centre immediatly.

Warnings

Keep out of reach of children.

Active Ingredient

Ethyl Alcohol 70% v/v

Other Information

Avoid extreme temperatures.

Purpose

Antibacterial

Uses

To decrease bacteria on the skin.

Front Label area

Requires no water or towels.
Apply small amount to hands and rub lightly until dry.